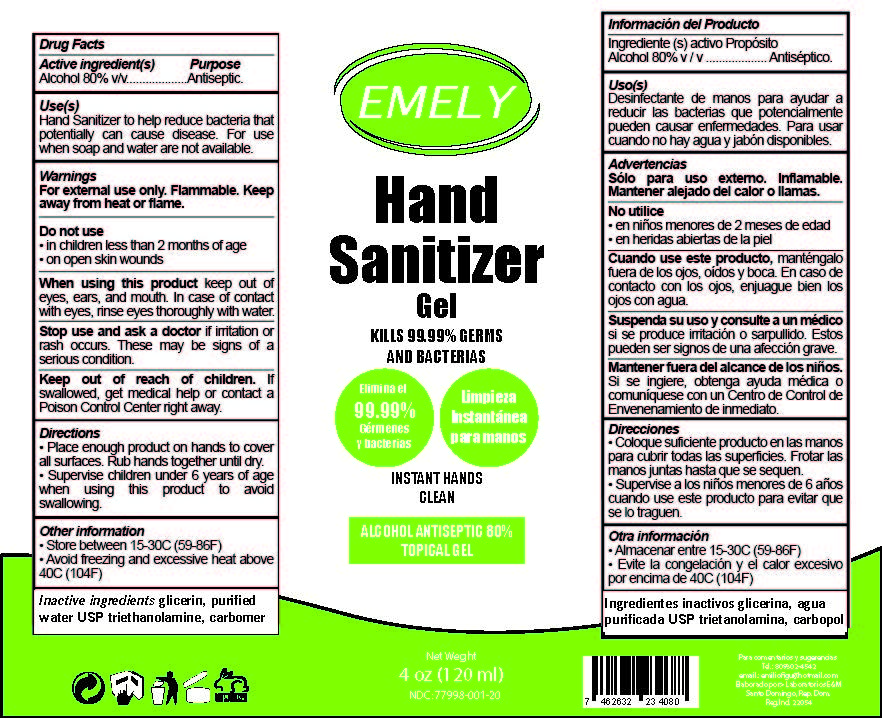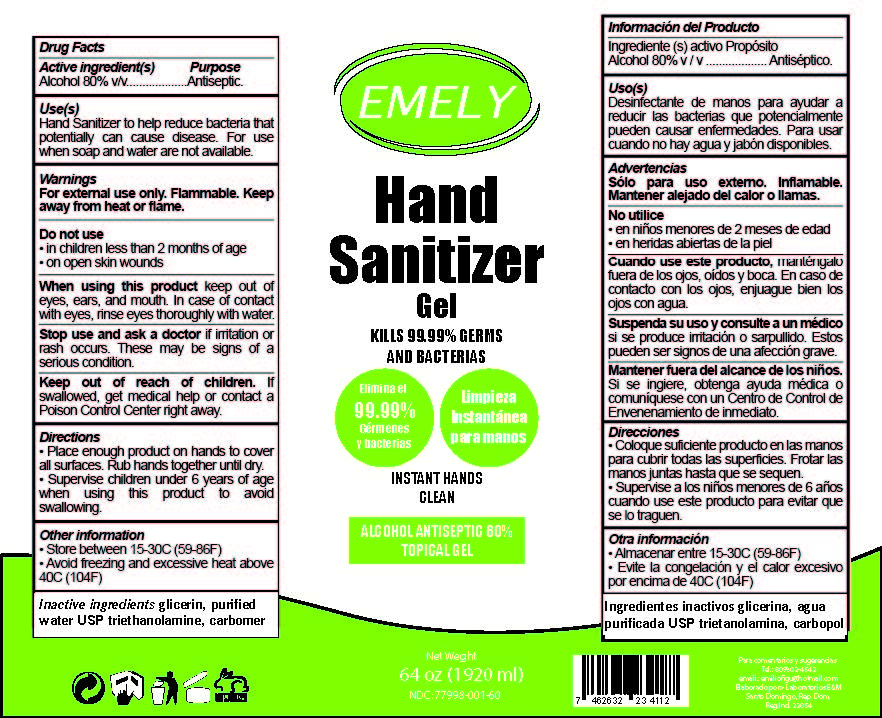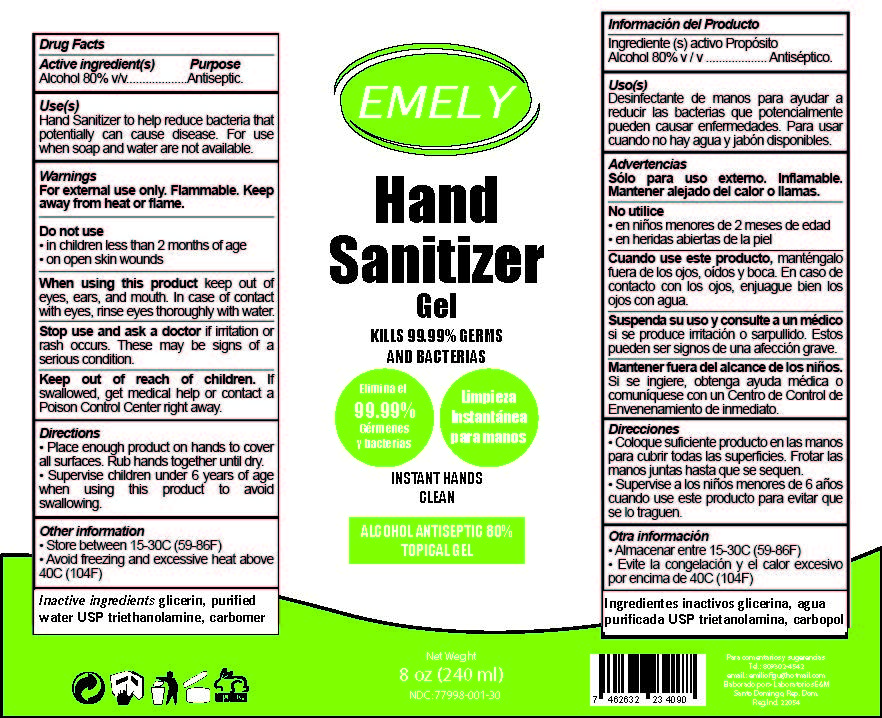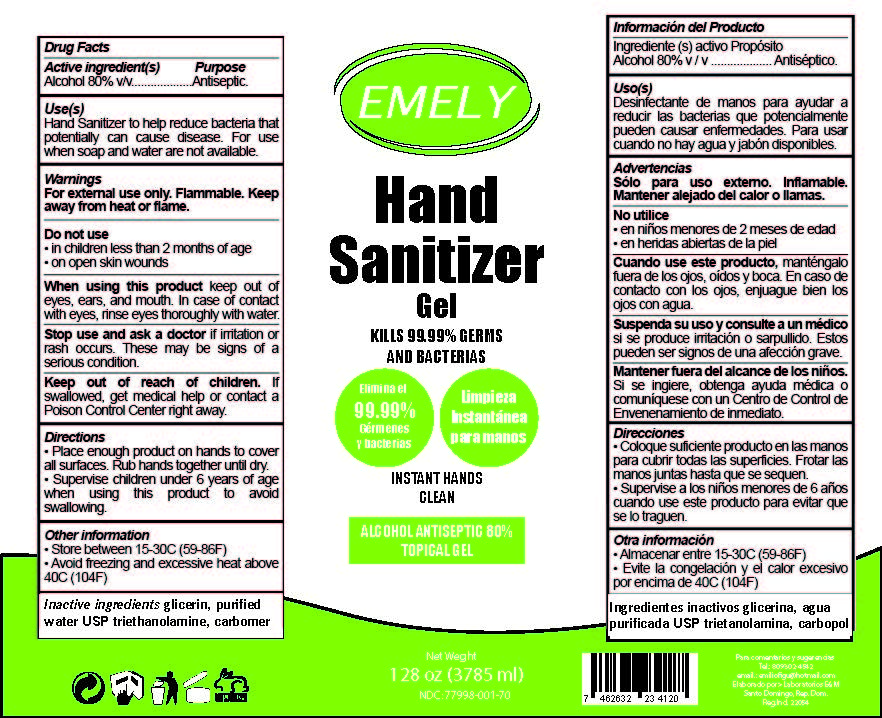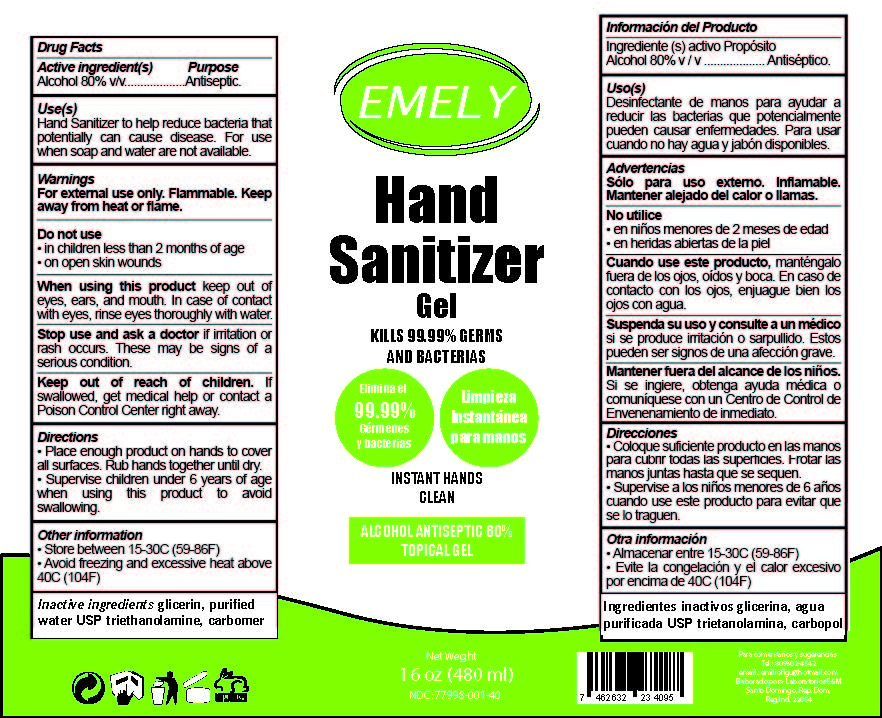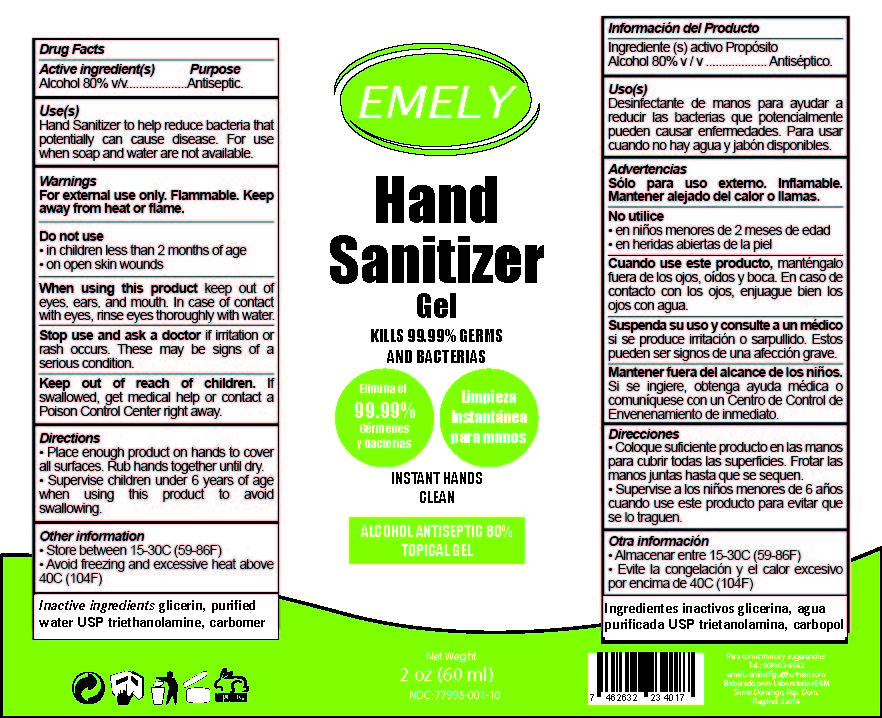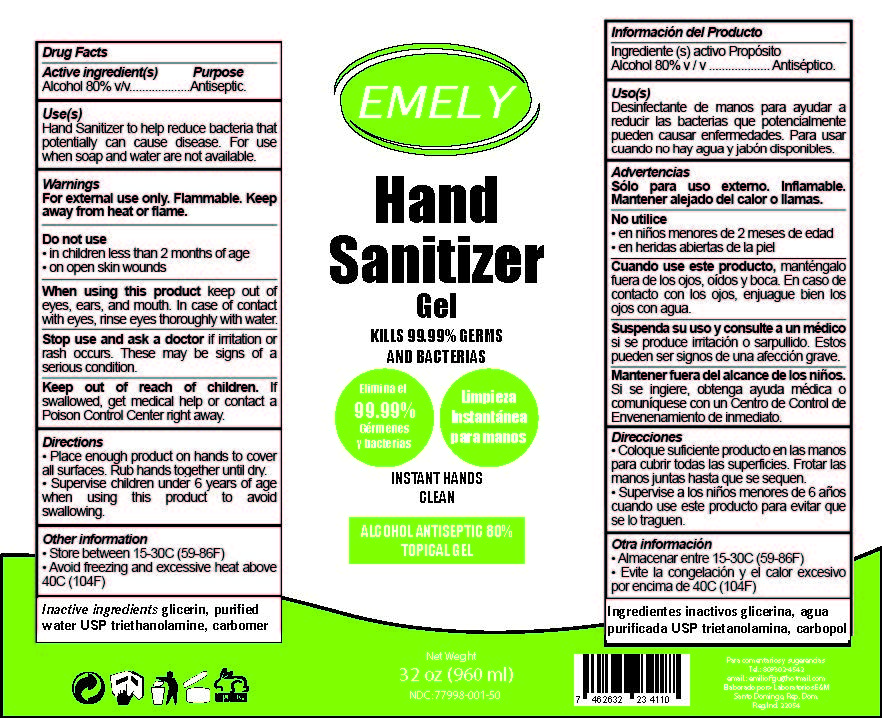 DRUG LABEL: Emely Hand Sanitizer
NDC: 77998-001 | Form: GEL
Manufacturer: Laboratorios E&M SRL
Category: otc | Type: HUMAN OTC DRUG LABEL
Date: 20211231

ACTIVE INGREDIENTS: ALCOHOL 80 mL/100 mL
INACTIVE INGREDIENTS: GLYCERIN; TROLAMINE; CARBOMER HOMOPOLYMER, UNSPECIFIED TYPE; WATER

Emely Hand Sanitizer (Gel)

Active Ingredient(s)

Alcohol 80% v/v Purpose: Antiseptic

Purpose

Aseptic, Hand Sanitizer

Uses

Hand Sanitizer to help reduce bacteria that potentially can cause disease. For use when soap and water are not available.

Warnings

For external use only. Flammable. Keep away from heat or flame.

Do not use

in children less than 2 months of age

on open skin wounds

When using this product keep out of eyes, ears, and mouth. In case of contact with eyes, rinse eyes thoroughly with water.

Stop use and ask a doctor if irritation or rash occurs. These may be signs of a serious condition.

Keep out of reach of children.If swallowed, get medical help or contact a Poison Control Center right away.

Directions

Place enough product on hands to cover all surfaces. Rub hands together until dry.

Supervise children under 6 years of age when using this product to avoid swallowing.

Other Information

Store between 15-30C (59-86F)

Avoid freezing and excessive heat above 40C (104F)

Inactive Ingredients

Glicerin, Purified Water USP, Triethanolamine, Carbomer

Package Label - Principal Display Panel

60 mL NDC: 77998-001-10

Package Label - Principal Display Panel

120 mL NDC: 77998-001-20

Package Label - Principal Display Panel

240 mL NDC: 77998-001-30

Package Label - Principal Display Panel

480 mL NDC: 77998-001-40

Package Label - Principal Display Panel

960 mL NDC: 77998-001-50

Package Label - Principal Display Panel

1920 mL NDC: 77998-001-60

Package Label - Principal Display Panel

3785 mL NDC: 77998-001-70